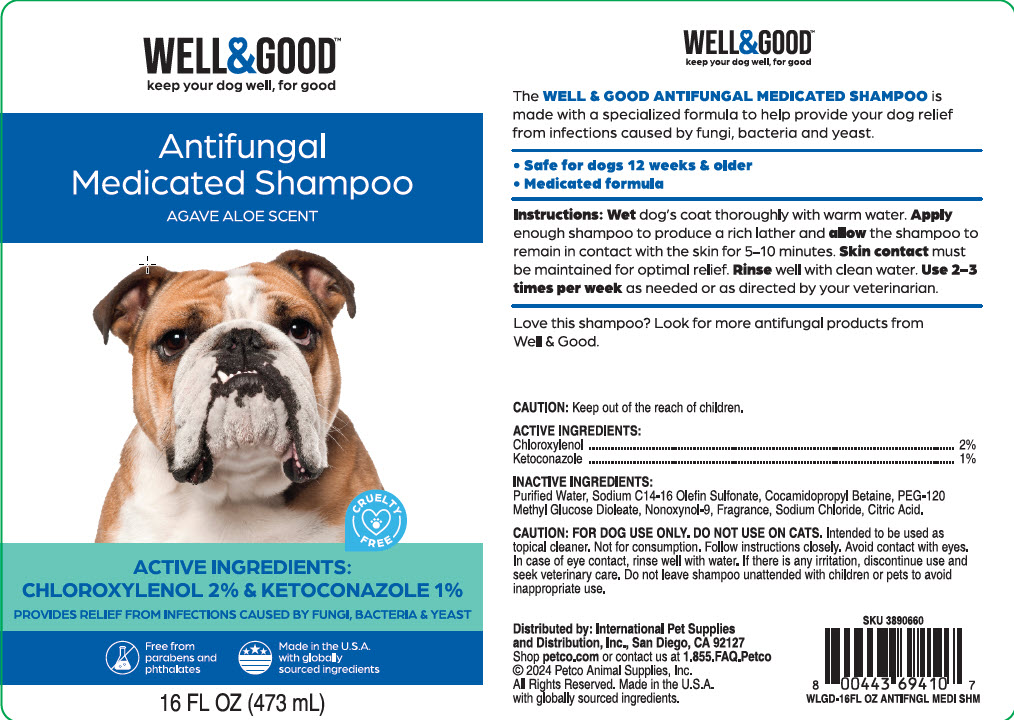 DRUG LABEL: Well and Good
NDC: 27102-581 | Form: SHAMPOO
Manufacturer: International Pet Supplies & Distribution
Category: animal | Type: OTC ANIMAL DRUG LABEL
Date: 20240913

ACTIVE INGREDIENTS: CHLOROXYLENOL 20 mg/473 mL
INACTIVE INGREDIENTS: KETOCONAZOLE 10 mg/473 mL

Antifungal Medicated Shampoo

Caution

FOR DOG USE ONLY. DO NOT USE ON CATS. Intended to be used as topical cleaner. Not for consumption. Follow instructions closely. Avoid contact with eyes. In case of eye contact, rinse well with water. If there is any irritation, discontinue use and seek veterinary care. Do not leave shampoo unattended with children or pets to avoid inappropriate use.

Instructions

Wet dog's coat thoroughly with warm water. Apply enough shampoo to produce a rich lather and allow the shampoo to remain in contact with the skin for 5-10 minutes. Skin contact must be maintained for optimal relief. Rinse well with clean water. Use 2-3 times per week as needed or as directed by your veterinarian.